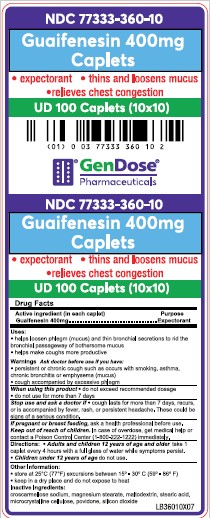 DRUG LABEL: GUAIFENESIN 400MG CAPLETS
NDC: 77333-360 | Form: TABLET
Manufacturer: Gendose Pharmaceuticals, LLC
Category: otc | Type: HUMAN OTC DRUG LABEL
Date: 20250702

ACTIVE INGREDIENTS: GUAIFENESIN 400 mg/1 1
INACTIVE INGREDIENTS: CROSCARMELLOSE SODIUM; MAGNESIUM STEARATE; MALTODEXTRIN; STEARIC ACID; MICROCRYSTALLINE CELLULOSE; POVIDONE; SILICON DIOXIDE

GENDOSE - GUAIFENESIN 400 mg CAPLETS (77333-360)

ACTIVE INGREDIENT (IN EACH CAPLET)

GUAIFENESIN 400MG

PURPOSE

EXPECTORANT

USES

- HELPS LOOSEN PHLEGM (MUCUS) AND THIN BRONCHIAL SECRETIONS TO RID THE BRONCHIAL PASSAGEWAY OF BOTHERSOME MUCUS.
- HELPS MAKE COUGHS MORE PRODUCTIVE

WARNINGS

ASK DOCTOR BEFORE USE IF YOU HAVE:

- PERSISTENT OR CHRONIC COUGH SUAH AS OCCURS WITH SMOKING, ASTHMA, CHRONIC BRONCHITIS OR EMPHASEMA (MUCUS)
- COUGH ACCOMPANIED BY EXCESSIVE PHLEGM

WHEN USING THIS PRODUCT

- DO NOT EXCEED RECOMMENDED DOSAGE
- DO NOT USE FOR MORE THAN 7 DAYS

STOP USE AND ASK A DOCTOR IS

- COUGH LASTS FOR MORE THAN 7 DAYS, RECURS, OR IS ACCOMPANIED BY FEVER, RASH, OR PERSISTENT HEADACHE. THESE COULD BE SIGNS OF A SERIOUS CONDITION.

IF PREGNANT OR BREAST FEEDING, ASK A HEALTH PROFESSIONAL BEFORE USE.

KEEP OUT OF REACH OF CHILDREN. IN CASE OF OVERDOSE, GET MEDICAL HELP OR CONTACT A POISON CONTROL CENTER (1-800-222-1222) IMMEDIATELY.

DIRECTIONS

- ADULTS AND CHILDREN 12 YEARS OF AGE AND OLDERTAKE 1 CAPLET EVERY 4 HOURS WITH A FULL GLASS OF WATER WHILE SYMPTOMS PERSIST.
- CHILDREN UNDER 12 YEARS OF AGEDO NOT USE.

OTHER INFORMATION

- STORE AT 25°C (77°F) EXCURSIONS BETWEEN 15° - 30° C (59° - 86°F)
- KEEP IN A DRY PLACE AND DO NOT EXPOSE TO HEAT

INACTIVE INGREDIENTS

CROSCARMELLOSE SODIUM, MAGNESIUM STEARATE, MALTODEXTRIN, STEARIC ACID, MICROCRYSTALLINE CELLULOSE, POVIDONE, SILICON DIOXIDE